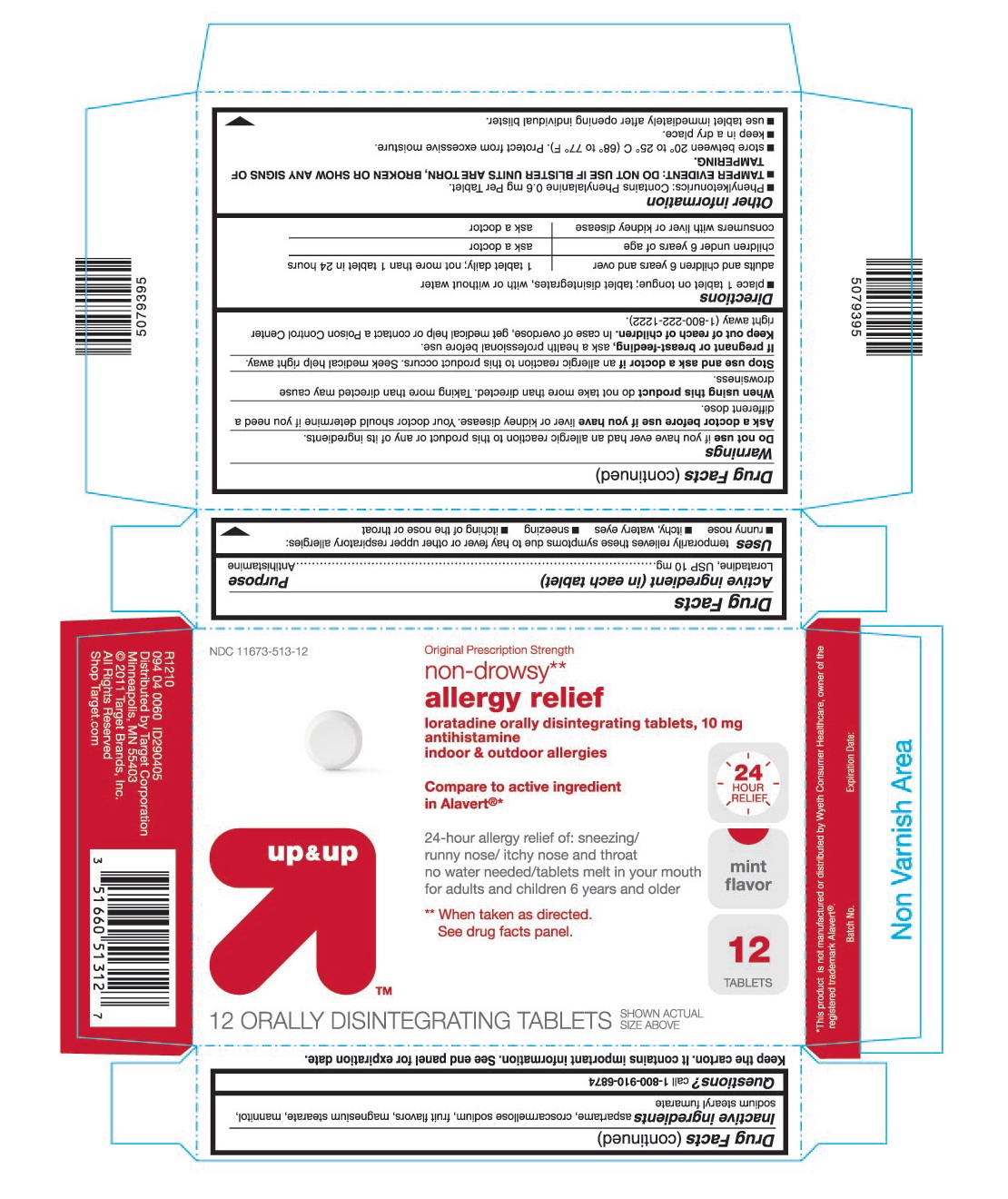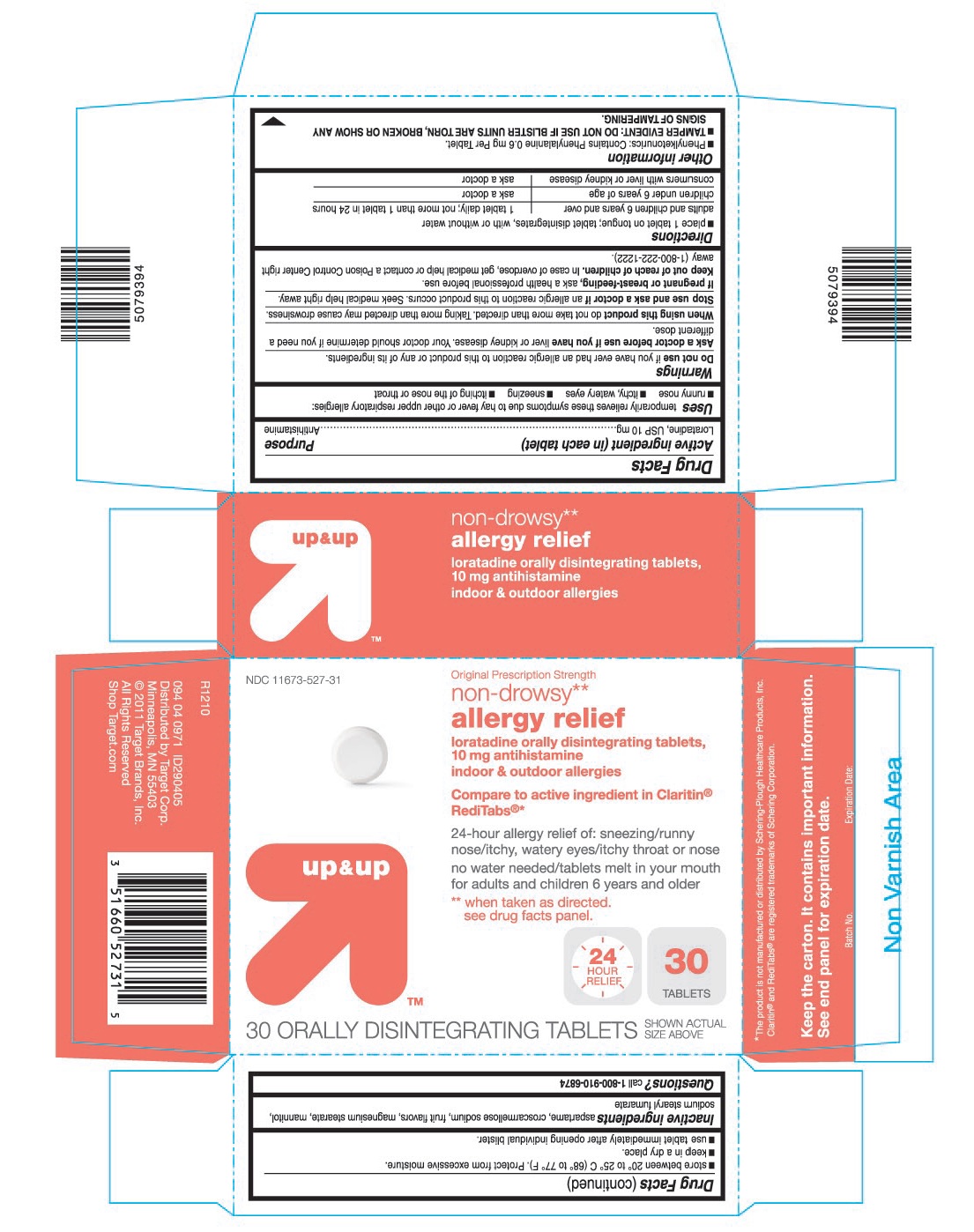 DRUG LABEL: Loratadine
NDC: 11673-513 | Form: TABLET, ORALLY DISINTEGRATING
Manufacturer: Target Corporation
Category: otc | Type: HUMAN OTC DRUG LABEL
Date: 20121005

ACTIVE INGREDIENTS: LORATADINE 10 mg/1 1
INACTIVE INGREDIENTS: ASPARTAME; CROSCARMELLOSE SODIUM; MAGNESIUM STEARATE; MANNITOL; SODIUM STEARYL FUMARATE

Drug Facts

ACTIVE INGREDIENT (IN EACH TABLET)

Loratadine, USP 10 mg

PURPOSE

Antihistamine

USES

Temporarily relieves these symptoms due to hay fever or other upper respiratory allergies:

- runny nose
- itchy, watery eyes
- sneezing
- itching of the nose or throat

WARNINGS

Do not use

If you have ever had an allergic reaction to this product or any of its ingredients.

Ask a doctor before use if you have

Liver or kidney disease. Your doctor should determine if you need a different dose.

When using this product

Do not take more than directed. Taking more than directed may cause drowsiness.

Stop use and ask a doctor if

An allergic reaction to this product occurs. Seek medical help right away.

If pregnant or breast-feeding

Ask a health professional before use.

Keep out of reach of children.

In case of overdose, get medical help or contact a Poison Control Center right away (1-800-222-1222).

DIRECTIONS

- place 1 tablet on tongue; tablet disintegrates, with or without water
  adults and children 6 years and over | 1 tablet daily; not more than 1 tablet in 24 hours
  children under 6 years of age | ask a doctor
  consumers with liver or kidney disease | ask a doctor

OTHER INFORMATION

- Phenylketonurics: Contains Phenylalanine 0.6 mg Per Tablet.
- TAMPER EVIDENT: DO NOT USE IF BLISTER UNITS ARE TORN, BROKEN OR SHOW ANY SIGNS OF TAMPERING.
- store between 20° to 25° C (68° to 77° F). Protect from excessive moisture.
- keep in a dry place.
- use tablet immediately after opening individual blister.

INACTIVE INGREDIENTS

aspartame, croscarmellose sodium, fruit flavors, magnesium stearate, mannitol, sodium stearyl fumarate

QUESTIONS?

Call 1-800-910-6874

PRINCIPAL DISPLAY PANEL

NDC 11673-513-12

Original Prescription Strength

non-drowsy**

allergy relief

loratadine orally disintegrating tablets, 10 mg

antihistamine

indoor & outdoor allergies

Compare to active ingredient in Alavert®*

24 HOUR RELIEF

24-hour allergy relief of: sneezing/

runny nose/itchy nose and throat

no water needed/tablets melt in your mouth

for adults and children 6 years and older

mint flavor

** When taken as directed.

See drug facts panel.

up & up™

12 ORALLY DISINTEGRATING TABLETS

Distributed by Target Corporation

5079395/R1210

Alavert - 12's

NDC 11673-527-31

Original Prescription Strength

non-drowsy**

allergy relief

loratadine orally disintegrating tablets,

10 mg antihistamine

indoor & outdoor allergies

Compare to active ingredient in Claritin® Reditabs®*

24-hour allergy relief of: sneezing/runny

nose/itchy, watery eyes/itchy throat or nose

no water needed/tablets melt in your mouth

for adults and children 6 years and older

** When taken as directed.

See drug facts panel.

up & up™

24 HOUR RELIEF

30 ORALLY DISINTEGRATING TABLETS

Distributed by Target Corp.

5079394/R1210

Claritin - 30's